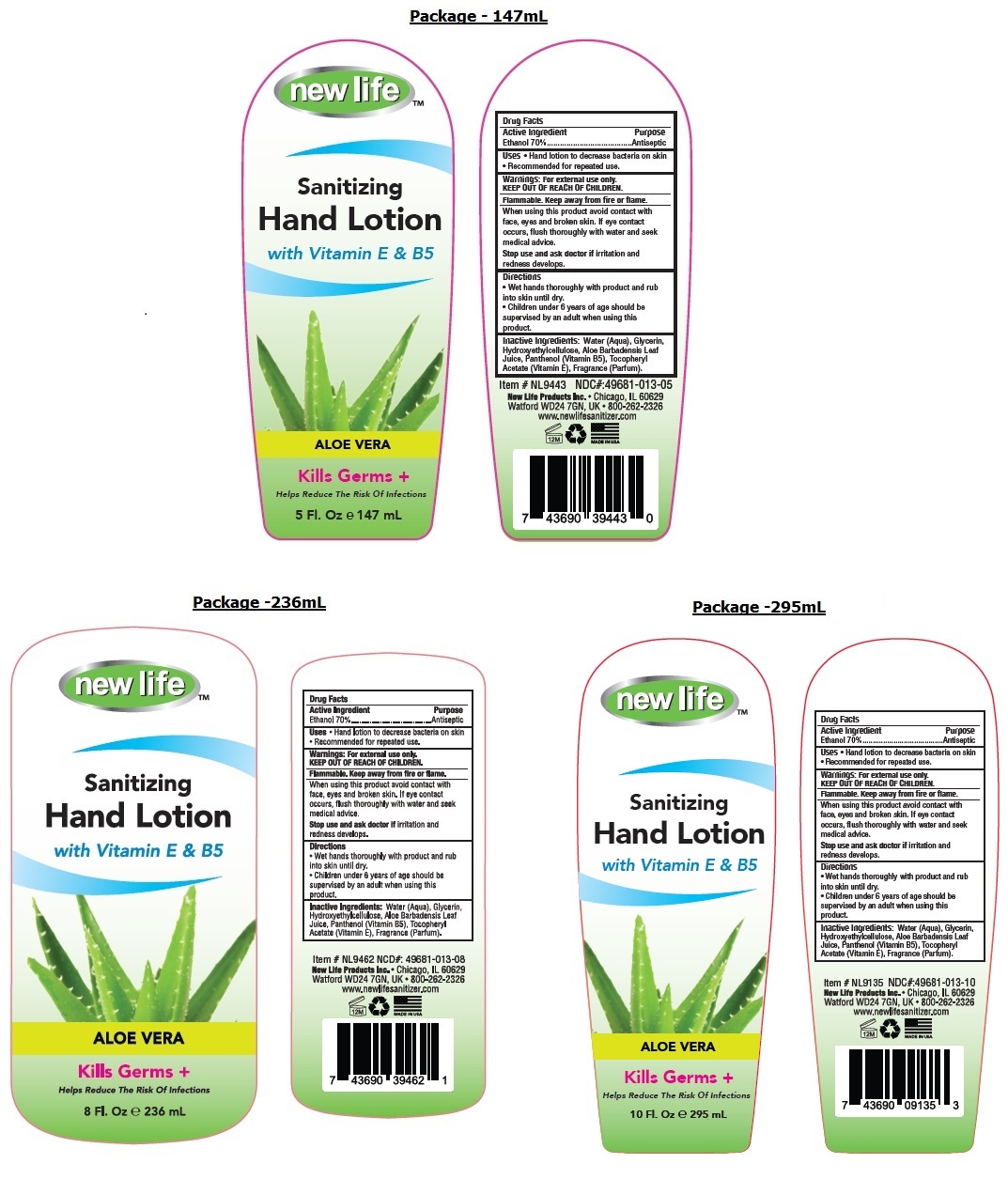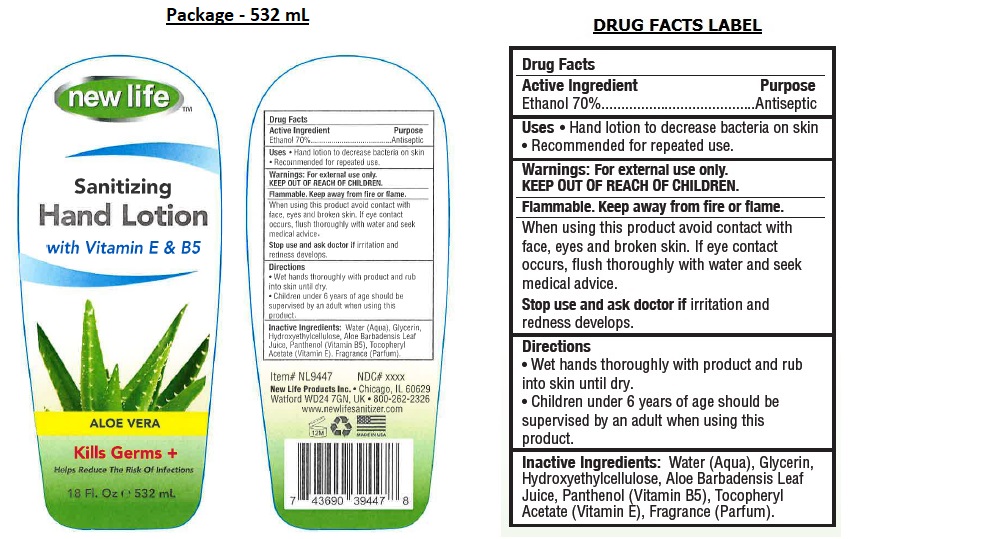 DRUG LABEL: New Life Sanitizing HandLotion with Vitamin E and B5- Aloe Vera
NDC: 49681-013 | Form: LOTION
Manufacturer: New Life Products, Inc.
Category: otc | Type: HUMAN OTC DRUG LABEL
Date: 20210702

ACTIVE INGREDIENTS: ALCOHOL 70 mL/100 mL
INACTIVE INGREDIENTS: WATER; GLYCERIN; HYDROXYETHYL CELLULOSE, UNSPECIFIED; ALOE VERA LEAF; PANTHENOL; .ALPHA.-TOCOPHEROL ACETATE

new lifeTM Sanitizing Hand Lotion with Vitamin E & B5 ALOE VERA

Active Ingredient

Ethanol 70%

Purpose

Antiseptic

Uses

• Hand lotion to decrease bacteria on skin • Recommended for repeated use

Warnings:

For external use only.

Flammable. Keep away from fire or flame.

When using this product avoid contact with face, eyes and broken skin. If eye contact occurs, flush thoroughly with water and seek medical advice.
Stop use and ask doctor if irritation and redness develops.

KEEP OUT OF REACH OF CHILDREN.

Directions

• Wet hands thoroughly with product and rub into skin until dry.
• Children under 6 years of age should be supervised by an adult when using this product.

Inactive Ingredients:

Water (Aqua), Glycerin, Hydroxyethylcellulose, Aloe Barbadensis Leaf Juice, Panthenol (Vitamin B5), Tocopheryl Acetate (Vitamin E), Fragrance (Parfum).

with Vitamin E & B5

ALOE VERA

Kills Germs +

Helps Reduce The Risk Of Infections

New Life Products, Inc. • Chicago, IL 60629

Watford WD24 7GN, UK • 800-262-2326

www.newslifesanitizer.com

MADE IN USA